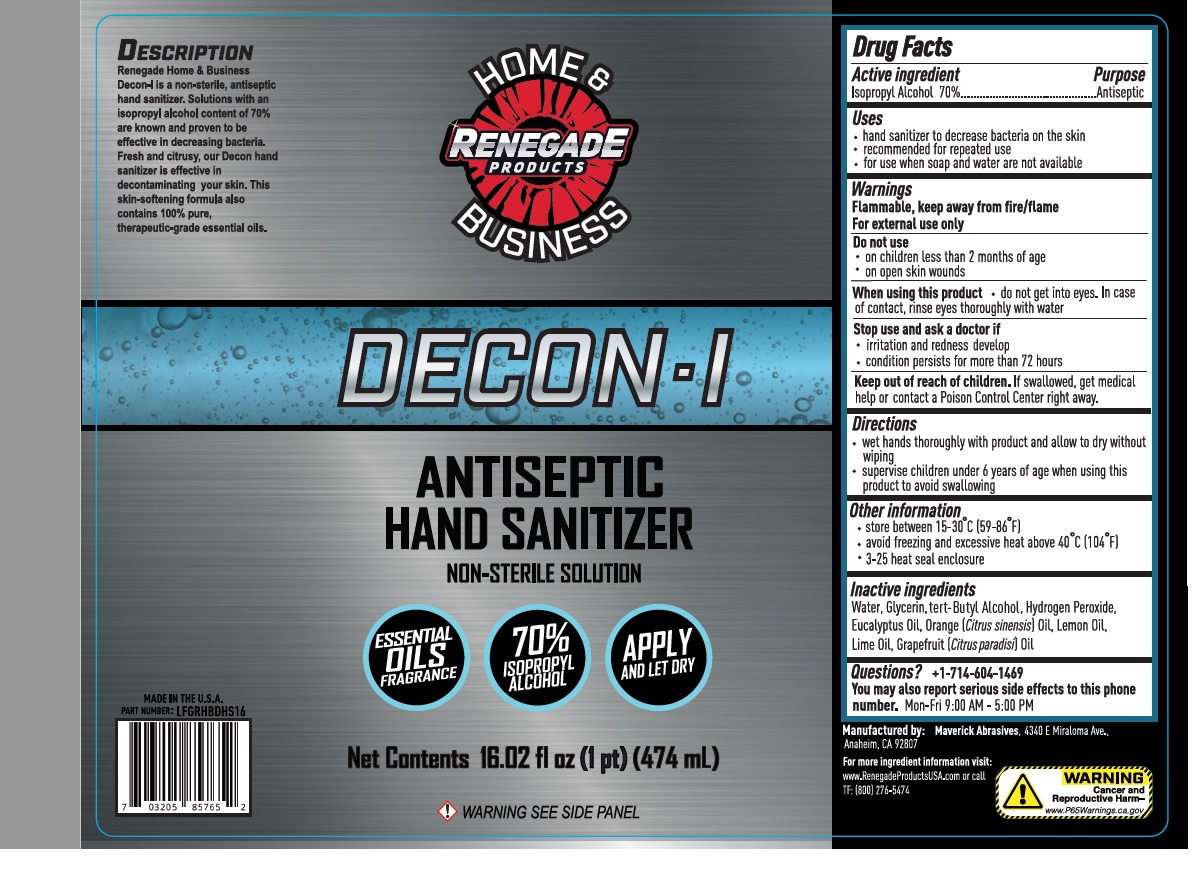 DRUG LABEL: Decon-I Antiseptic Hand Sanitizer
NDC: 73837-651 | Form: SOLUTION
Manufacturer: Maverick Abrasives Corporation
Category: otc | Type: HUMAN OTC DRUG LABEL
Date: 20220128

ACTIVE INGREDIENTS: ISOPROPYL ALCOHOL 70 mL/100 mL
INACTIVE INGREDIENTS: WATER; GLYCERIN; TERT-BUTYL ALCOHOL; HYDROGEN PEROXIDE; EUCALYPTUS OIL; ORANGE OIL; LEMON OIL; LIME OIL; GRAPEFRUIT OIL

DECON - I ANTISEPTIC HAND SANITIZER

Active ingredient

Isopropyl Alcohol 70%

Purpose

Antiseptic

Uses

- hand sanitizer to decrease bacteria on the skin
- recommended for repeated use
- for use when soap and water are not available

Warnings

Flammable, keep away from fire/flame

For external use only

Do not use

- on children less than 2 months of age
- on open skin wounds

When using this product

- do not get into eyes. In case of contact, rinse eyes thoroughly with water

Stop use and ask a doctor if

- irritation and redness develop
- condition persists for more than 72 hours

Keep out of reach of children. If swallowed, get medical help or contact a Poison Control Center right away.

Directions

- wet hands thoroughly with product and allow to dry without wiping
- supervise children under 6 years of age when using this product to avoid swallowing

Other information

- store between 15-30°C (59-86°F)
- avoid freezing and excessive heat above 40°C (104°F)
- 3-25 heat seal enclosure

Inactive Ingredients

Water, Glycerin, tert-Butyl Alcohol, Hydrogen Peroxide, Eucalyptus Oil, Orange (Citrus sinensis) Oil, Lemon Oil, Lime Oil, Grapefruit (Citrus paradisi) Oil

Questions?

+1-714-604-1469

You may also report serious side effects to this phone number. Mon-Fri 9:00AM-5:00 PM

NON-STERILE SOLUTION

ESSENTIAL OILS FRAGRANCE

70% ISOPROPYL ALCOHOL

APPLY AND LET DRY

WARNING SEE SIDE PANEL

DESCRIPTION

Renegade Home & Business Decon-I is a non-sterile, antiseptic hand sanitizer. Solutions with an isopropyl alcohol content of 70% are known and proven to be effective in decreasing bacteria. Fresh and citrusy, our Decon hand sanitizer is effective in decontaminating your skin. This skin-softening formula also contains 100% pure, therapeutic-grade essential oils.

MADE IN THE U.S.A

Manufactured by: Maverick Abrasives, 4340 E Miraloma Ave.,
Anaheim, CA 92807

For more ingredient information visit:
www.RenegadeProductsUSA.com or call
TF: [800] 276-5474

WARNING

Cancer and Reproductive Harm

www.P65Warnings.ca.gov